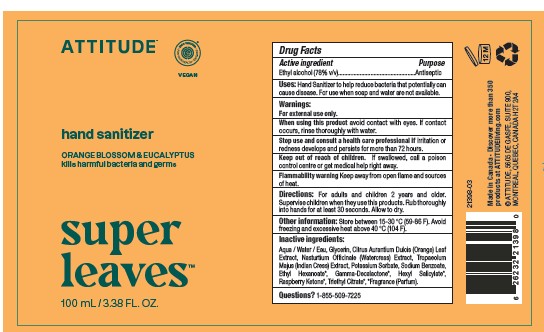 DRUG LABEL: ATTITUDE Super Leaves Hand Sanitizer Orange Leaves
NDC: 61649-893 | Form: SOLUTION
Manufacturer: 9055-7588 Quebec Inc. DBA Attitude
Category: otc | Type: HUMAN OTC DRUG LABEL
Date: 20251020

ACTIVE INGREDIENTS: ALCOHOL 78.8 mL/100 mL
INACTIVE INGREDIENTS: CITRUS SINENSIS LEAF; NASTURTIUM OFFICINALE; TROPAEOLUM MAJUS; 4-(P-HYDROXYPHENYL)-2-BUTANONE; TRIETHYL CITRATE; POTASSIUM SORBATE; HEXYL SALICYLATE; WATER; SODIUM BENZOATE; GLYCERIN; ETHYL CAPROATE; .GAMMA.-DECALACTONE

ATTITUDE Super Leaves Hand Sanitizer - Orange Leaves

DRUG FACTS

ACTIVE INGREDIENT

Ethyl alcohol 78%(v/v)

PURPOSE

Antiseptic

INDICATIONS AND USAGE

Hand Sanitizer to help reduce bacteria that potentially can cause disease. For use when soap and water are not available.

WARNINGS

For external use only.

When using this product avoid contact with eyes. If contact occurs, rinse thoroughly with water.

Stop use and consult a health care professional if irritation or redness develops and persists for more than 72 hours.

Keep out of reach of children.If swallowed, call a poison control centre or get medical help right away.

Flammability warning. Keep away from open flame and sources of heat.

DOSAGE AND ADMINISTRATION

Directions: For adults and children 2 years and older. Supervise children when they use this products. Rub thoroughly into hands
for at least 30 seconds. Allow to dry.

Other information: Store between 15-30 °C (59-86 F). Avoid freezing and excessive heat above 40 °C (104 F).

INACTIVE INGREDIENT

Aqua / Water / Eau, Glycerin, Citrus Aurantium Dulcis (Orange) Leaf Extract, Nasturtium Officinale (Watercress) Extract, Tropaeolum
Majus (Indian Cress) Extract, Potassium Sorbate, Sodium Benzoate, Ethyl Hexanoate*, Gamma-Decalactone*, Hexyl Salicylate*, Raspberry Ketone*, Triethyl Citrate*, *Fragrance (Parfum).

Questions? 1-855-509-7225

PACKAGE LABEL

ATTITUDE

Super leaves

hand sanitizer

Orange leaves

kills harmful bacteria and germs

EWG verified

Vegan

100 ml / 3.38 fl.oz.

Made in Canada · Discover more than 350 products at ATTITUDEliving.com

© 2023 ATTITUDE, 5605 DE GASPE, SUITE 900,
MONTREAL, QUEBEC, CANADA H2T 2A4